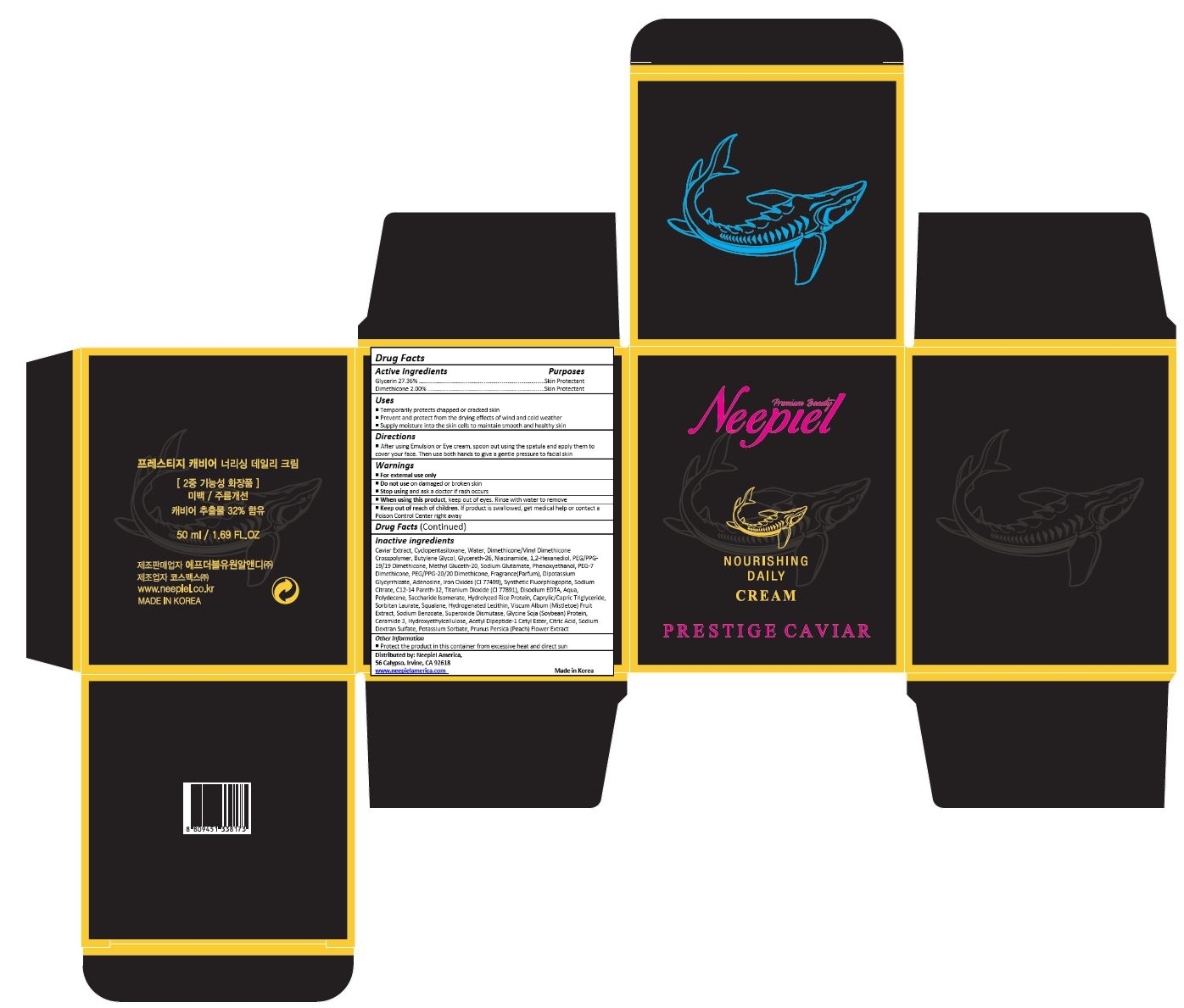 DRUG LABEL: Prestige Caviar Nourishing Daily Cream
NDC: 70519-004 | Form: CREAM
Manufacturer: FW1 R&D_Branch
Category: otc | Type: HUMAN OTC DRUG LABEL
Date: 20170627

ACTIVE INGREDIENTS: GLYCERIN 13.7 mg/50 mL; DIMETHICONE 1 mg/50 mL
INACTIVE INGREDIENTS: CAVIAR, UNSPECIFIED; CYCLOMETHICONE 5; WATER; DIMETHICONE/VINYL DIMETHICONE CROSSPOLYMER (HARD PARTICLE); BUTYLENE GLYCOL; GLYCERETH-26; NIACINAMIDE; 1,2-HEXANEDIOL; PEG/PPG-19/19 DIMETHICONE; METHYL GLUCETH-20; MONOSODIUM GLUTAMATE; PHENOXYETHANOL; PEG/PPG-20/20 DIMETHICONE; GLYCYRRHIZINATE DIPOTASSIUM; ADENOSINE; FERROSOFERRIC OXIDE; SODIUM CITRATE, UNSPECIFIED FORM; C12-14 PARETH-12; TITANIUM DIOXIDE; EDETATE DISODIUM; HYDROGENATED DIDECENE; SACCHARIDE ISOMERATE; MEDIUM-CHAIN TRIGLYCERIDES; SORBITAN MONOLAURATE; SQUALANE; HYDROGENATED SOYBEAN LECITHIN; VISCUM ALBUM FRUIT; SODIUM BENZOATE; LEDISMASE; SOY PROTEIN; CERAMIDE NP; HYDROXYETHYL CELLULOSE (100 MPA.S AT 2%); ACETYL TYROSYLARGININE CETYL ESTER; CITRIC ACID MONOHYDRATE; POTASSIUM SORBATE; PRUNUS PERSICA FLOWER

Drug Facts

ACTIVE INGREDIENT

Glycerin 27.36%
Dimethicone 2.00%

PURPOSE

Skin Protectant

INDICATIONS AND USAGE

Helps to prevent dehydration of skin

DOSAGE AND ADMINISTRATION

Apply liberally as needed onto skin

WARNINGS

For external use only.
Do not use on damaged or broken skin.
When using this product, keep out of eyes. Rinse with water to remove
Stop using and ask a doctor if rash occurs.

Keep out of reach of children.

If product is swallowed, get medical help or contact a Poison Control Center right away.

INACTIVE INGREDIENT

Caviar Extract, Cyclopentasiloxane, Water, Dimethicone/Vinyl Dimethicone Crosspolymer, Butylene Glycol, Glycereth-26, Niacinamide, 1,2-Hexanediol, PEG/PPG-19/19 Dimethicone, Methyl Gluceth-20, Sodium Glutamate, Phenoxyethanol, PEG-7 Dimethicone, PEG/PPG-20/20 Dimethicone, Fragrance(Parfum), Dipotassium Glycyrrhizate, Adenosine, Iron Oxides (CI 77499), Synthetic Fluorphlogopite, Sodium Citrate, C12-14 Pareth-12, Titanium Dioxide (CI 77891), Disodium EDTA, Aqua, Polydecene, Saccharide Isomerate, Hydrolyzed Rice Protein, Caprylic/Capric Triglyceride, Sorbitan Laurate, Squalane, Hydrogenated Lecithin, Viscum Album (Mistletoe) Fruit Extract, Sodium Benzoate, Superoxide Dismutase, Glycine Soja (Soybean) Protein, Ceramide 3, Hydroxyethylcellulose, Acetyl Dipeptide-1 Cetyl Ester, Citric Acid, Sodium Dextran Sulfate, Potassium Sorbate, Prunus Persica (Peach) Flower Extract